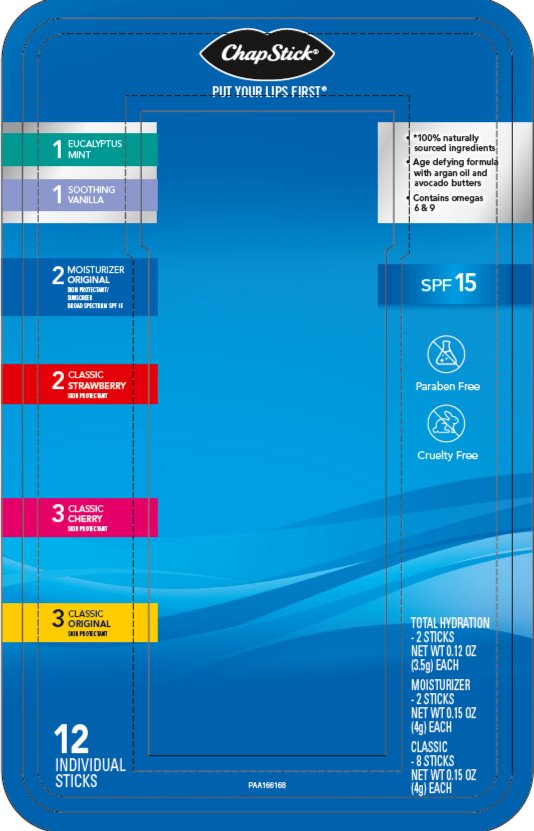 DRUG LABEL: Chapstick
NDC: 0573-2027 | Form: KIT | Route: TOPICAL
Manufacturer: Haleon US Holdings LLC
Category: otc | Type: HUMAN OTC DRUG LABEL
Date: 20240501

ACTIVE INGREDIENTS: AVOBENZONE 30 mg/1 g; OCTINOXATE 75 mg/1 g; PETROLATUM 423 mg/1 g; PETROLATUM 450 mg/1 g; PETROLATUM 450 mg/1 g; PETROLATUM 450 mg/1 g
INACTIVE INGREDIENTS: ALOE VERA LEAF; CARNAUBA WAX; CETYL ALCOHOL; .ALPHA.-TOCOPHEROL LINOLEATE, D-; ISOCETYL STEARATE; LANOLIN; MINERAL OIL; PARAFFIN; SACCHARIN; .ALPHA.-TOCOPHEROL ACETATE; WHITE WAX; ARACHIDYL PROPIONATE; CAMPHOR (NATURAL); CARNAUBA WAX; CETYL ALCOHOL; ISOPROPYL MYRISTATE; LANOLIN; LEMON OIL, COLD PRESSED; LIGHT MINERAL OIL; MALTOL; OCTYLDODECANOL; PARAFFIN; PHENYL TRIMETHICONE; D&C RED NO. 6; SACCHARIN; WHITE WAX; ARACHIDYL PROPIONATE; CAMPHOR (NATURAL); CARNAUBA WAX; CETYL ALCOHOL; ISOPROPYL MYRISTATE; LANOLIN; LIGHT MINERAL OIL; LEVOMENTHOL; OCTYLDODECANOL; PARAFFIN; PHENYL TRIMETHICONE; D&C RED NO. 6; SACCHARIN; WHITE WAX; ARACHIDYL PROPIONATE; CAMPHOR (NATURAL); CARNAUBA WAX; CETYL ALCOHOL; ISOPROPYL MYRISTATE; LANOLIN; LIGHT MINERAL OIL; OCTYLDODECANOL; OLEYL ALCOHOL; PARAFFIN; PHENYL TRIMETHICONE; D&C RED NO. 6; TITANIUM DIOXIDE; WHITE WAX; FD&C YELLOW NO. 5

Drug Facts

Moisturizer 2 in 1 Lip Care | Original

Active ingredients

Avobenzone 3%

Octinoxate 7.5%

White petrolatum 42.3%

Purposes

Sunscreens

Skin protectant

Uses

- helps prevent sunburn
- if used as directed with other sun protection measures (see Directions), decreases the risk of skin cancer and early skin aging caused by the sun
- helps prevent and temporarily protects chafed, chapped or cracked lips
- helps prevent and protect from the drying effects of wind and cold weather

Warnings

For external use only

Do not useon damaged or broken skin

Stop use and ask a doctor ifrash occurs

WHEN USING

When using this productkeep out of eyes. Rinse with water to remove.

Keep out of reach of children.If swallowed, get medical help or contact a Poison Control Center right away.

Directions

- apply liberally 15 minutes before sun exposure
- reapply at least every 2 hours
- use a water resistant sunscreen if swimming or sweating
- children under 6 months of age: Ask a doctor
- Sun Protection Measures.Spending time in the sun increases your risk of skin cancer and early skin aging. To decrease this risk, regularly use a sunscreen with a Broad Spectrum SPF value of 15 or higher and other sun protection measures including:
  - limited time in the sun, especially from 10 a.m. – 2 p.m.
  - wear long-sleeved shirts, pants, hats, and sunglasses

Other Information

- store at 20-25°C (68-77°F)
- protect this product from excessive heat and direct sun

Inactive ingredients

aloe barbadensis leaf extract, carnauba wax, cetyl alcohol, fragrance, isocetyl stearate, isopropyl lanolate, lanolin, mineral oil, paraffin, saccharin, tocopheryl linoleate/oleate, vitamin E acetate, white wax

Questions or Comments?

call weekdays from 9 AM to 5 PM EST at 1-877-227-3421

Classic | Original . Cherry . Strawberry

Active ingredient

White petrolatum 45%

Purpose

Skin protectant

Uses

- helps prevent and temporarily protects chafed, chapped or cracked lips
- helps prevent and protect from the drying effects of wind and cold weather

Warnings

For external use only

Directions

Apply as needed

Other Information

store at 20-25°C (68-77°F)

Inactive ingredients (Original)

arachidyl propionate, camphor, carnauba wax, cetyl alcohol, fragrance, isopropyl lanolate, isopropyl myristate, lanolin, light mineral oil, octyldodecanol, oleyl alcohol, paraffin, phenyl trimethicone, red 6 lake, titanium, white wax, yellow 5 lake

Inactive ingredients (Cherry)

arachidyl propionate, camphor, carnauba wax, cetyl alcohol, fragrance, isopropyl lanolate, isopropyl myristate, lanolin, light mineral oil, menthol, octyldodecanol, paraffin, phenyl trimethicone, red 6 lake, saccharin, white wax

Inactive ingredients (Strawberry)

arachidyl propionate, camphor, carnauba wax, cetyl alcohol, fragrance, isopropyl lanolate, isopropyl myristate, lanolin, lemon oil, light mineral oil, maltol, octyldodecanol, paraffin, phenyl trimethicone, red 6 lake, saccharin, white wax

Chapstick total hydration Eucalyptus Mint

Ingredients:

helianthus annuus (sunflower) seed oil, jojoba esters, euphorbia cerifera (candelilla) wax, cocos nucifera (coconut) oil, beeswax, caprylic/capric triglyceride, copernicia cerifera (carnauba) wax,

argania spinosa (argan) kernel oil, flavor, tocopheryl acetate, carthamus tinctorius (safflower) seed oil, mangifera indica (mango) seed butter, butyrospermum parkii (shea) butter, octyldodecanol, persea gratissima (avocado) oil, olea europaea (olive) fruit oil, tocopherol, hydrogenated soybean oil, aloe barbadensis leaf extract, rubus idaeus (raspberry) seed oil, glyceryl stearate

Other information

store at 20-25°C (68-77°F).

Chapstick total hydration Soothing Vanilla

Ingredients:

helianthus annuus (sunflower) seed oil, jojoba esters, euphorbia cerifera (candelilla) wax, cocos nucifera (coconut) oil, beeswax, caprylic/capric triglyceride, copernicia cerifera (carnauba) wax,

argania spinosa (argan) kernel oil, flavor, tocopheryl acetate, carthamus tinctorius (safflower) seed oil, mangifera indica (mango) seed butter, butyrospermum parkii (shea) butter, octyldodecanol, persea gratissima (avocado) oil, olea europaea (olive) fruit oil, tocopherol, hydrogenated soybean oil, aloe barbadensis leaf extract, rubus idaeus (raspberry) seed oil, glyceryl stearate

Other information

store at 20-25°C (68-77°F).

Additional Information

Paraben Free . Cruelty Free

Distributed by: GSK Consumer Healthcare, Warren, NJ 07059

For most recent product information, visit www.chapstick.com

Trademarks owned or licensed by GSK ©2021 GSK or licensor

Patents: www.productspats.com

PRINCIPAL DISPLAY PANEL

NDC 0573-2027-01

ChapStick®

PUT YOUR LIPS FIRST®

1 EUCALYPTUS MINT

1 SOOTHING VANILLA

- *100% naturally sourced ingredients
- Age defying formula with argan oil and avocado butters
- Contains omegas 6 & 9

2 MOISTURIZER ORIGINAL
SKIN PROTECTANT / SUNSCREEN
BROAD SPECTRUM SPF 15

SPF 15

2 CLASSIC STRAWBERRY
SKIN PROTECTANT

3 CLASSIC CHERRY
SKIN PROTECTANT

Paraben Free

Cruelty Free

3 CLASSIC ORIGINAL
SKIN PROTECTANT

12 INDIVIDUAL STICKS
TOTAL HYDRATION

-2 STICKS
NET WT 0.12 OZ
(3.5g) EACH

MOISTURIZER
-2 STICKS
NET WT 0.15 OZ
(4g) EACH

CLASSIC
-8 STICKS
NET WT 0.15 OZ
(4g) EACH

PAA166168 – Front